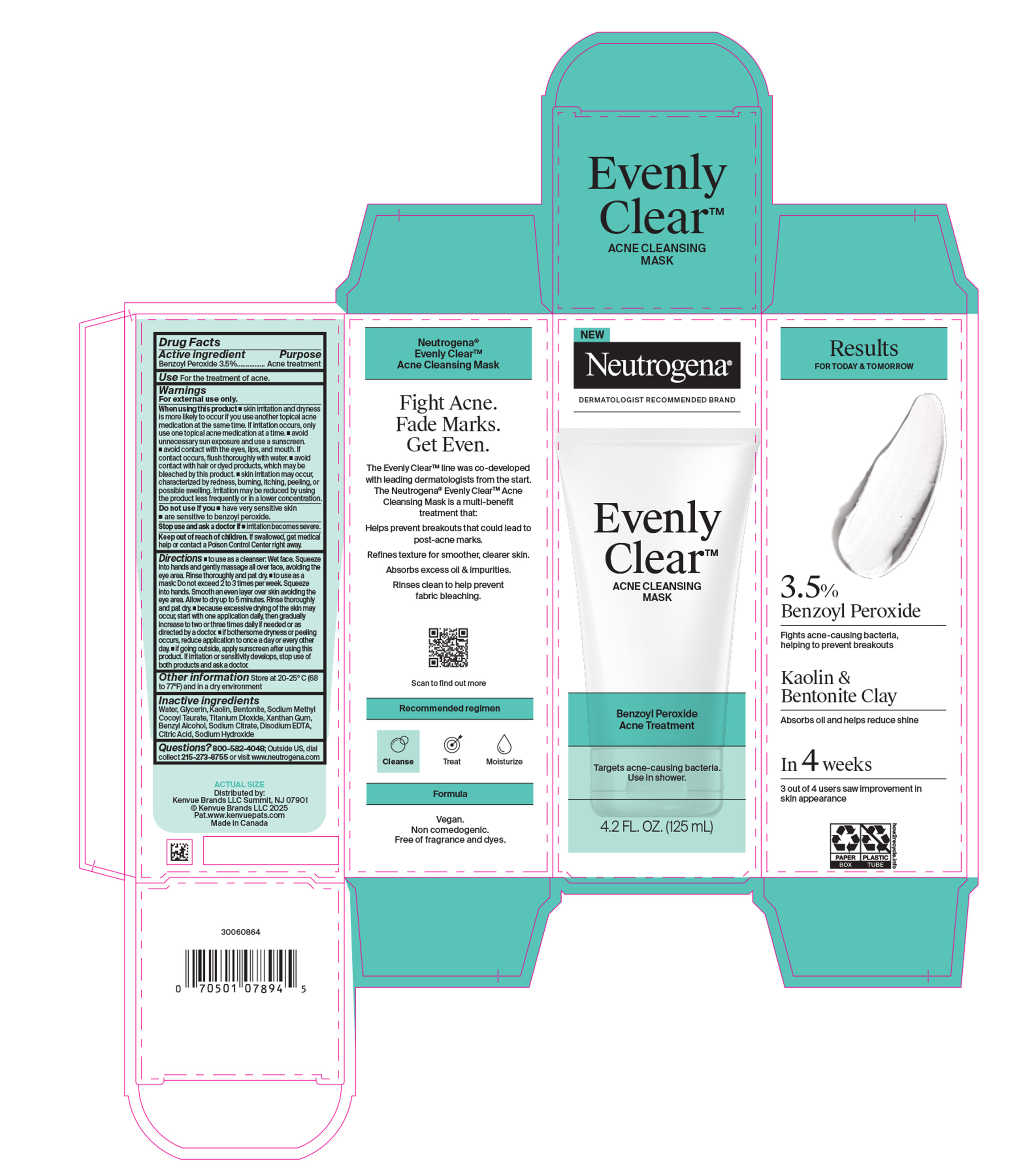 DRUG LABEL: Neutrogena Evenly Clear Acne Cleansing Mask
NDC: 69968-0943 | Form: PASTE
Manufacturer: Kenvue Brands LLC
Category: otc | Type: HUMAN OTC DRUG LABEL
Date: 20250917

ACTIVE INGREDIENTS: BENZOYL PEROXIDE 35 mg/1 mL
INACTIVE INGREDIENTS: KAOLIN; GLYCERIN; BENTONITE; SODIUM METHYL COCOYL TAURATE; TITANIUM DIOXIDE; XANTHAN GUM; BENZYL ALCOHOL; SODIUM CITRATE; SODIUM HYDROXIDE; EDETATE DISODIUM; WATER; CITRIC ACID

Neutrogena Evenly Clear Acne Cleansing Mask

Drug Facts

Active Ingredient

Benzoyl Peroxide (3.5%)

Purpose

.Acne treatment

Use

For the treatment of acne.

Warnings

For external use only.

When using this product

▪ skin irritation and dryness is more likely to occur if you use another topical acne medication at the same time. If irritation occurs, only use one topical acne medication at a time. ▪ avoid unnecessary sun exposure and use a sunscreen.▪ avoid contact with the eyes, lips, and mouth. If contact occurs, flush thoroughly with water. ▪ avoid contact with hair or dyed products, which may be bleached by this product. ▪ skin irritation may occur, characterized by redness, burning, itching, peeling, or possible swelling. Irritation may be reduced by using the product less frequently or in a lower concentration.

Do not use if you

- have very sensitive skin.
- are sensitive to benzoyl peroxide.

Stop use and ask a doctor if

- irritation becomes severe.

Keep out of reach of children. If swallowed, get medical help or contact a Poison Control Center right away.

Directions

▪ to use as a cleanser: Wet face. Squeeze into hands and gently massage all over face, avoiding the eye area. Rinse thoroughly and pat dry.

▪ to use as a mask: Do not exceed 2 to 3 times per week. Squeeze into hands. Smooth an even layer over skin avoiding the eye area. Allow to dry up to 5 minutes. Rinse thoroughly and pat dry.

▪ because excessive drying of the skin may occur, start with one application daily, then gradually increase to two or three times daily if needed or as directed by a doctor.

▪ if bothersome dryness or peeling occurs, reduce application to once a day or every other day.

▪ if going outside, apply sunscreen after using this product. If irritation or sensitivity develops, stop use of both products and ask a doctor.

Other Information

Store at 20-25°C (68 to 77°F) and in a dry environment

Inactive Ingredients

Water, Glycerin, Kaolin, Bentonite, Sodium Methyl Cocoyl Taurate, Titanium Dioxide, Xanthan Gum, Benzyl Alcohol, Sodium Citrate, Disodium EDTA, Citric Acid, Sodium Hydroxide

Questions?

800-582-4048; Outside US, dial collect 215-273-8755 or visit www.neutrogena.com

Distributed by:

Kenvue Brands LLC

Summit, NJ 07901

PRINCIPAL DISPLAY PANEL - 125 mL Tube Label

NEW

Neutrogena®

DERMATOLOGIST RECOMMENDED BRAND

Evenly

ClearTM

ACNE CLEANSING

MASK

Benzoyl Peroxide

Acne Treatment

Targets acne-causing bacteria.

Use in shower.

4.2 FL. OZ. (125 mL)